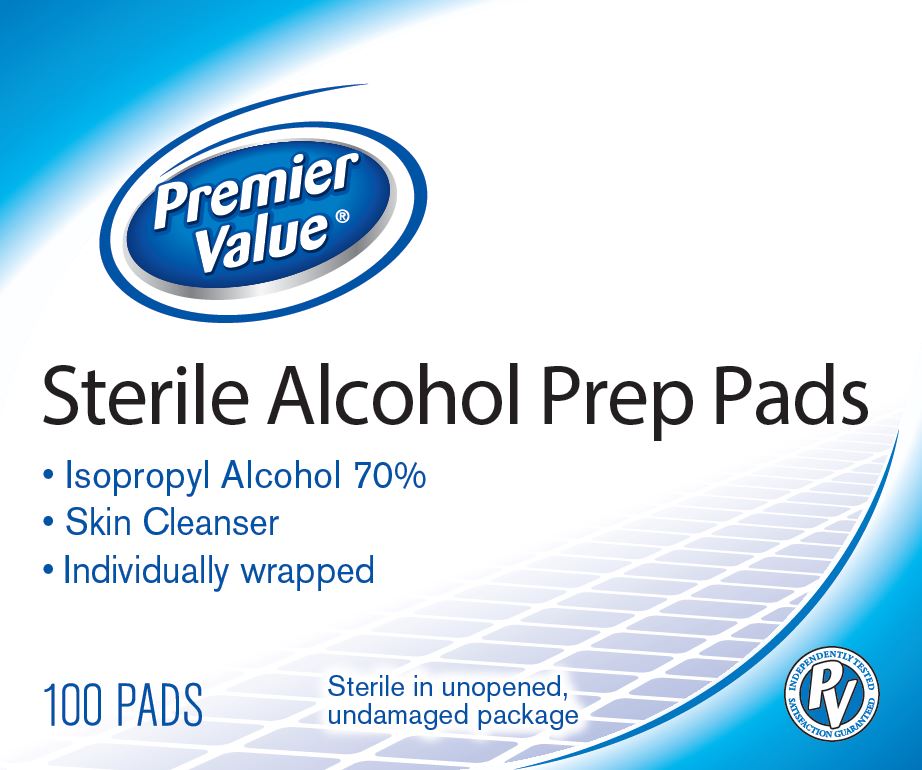 DRUG LABEL: Premier Value
NDC: 68016-809 | Form: SWAB
Manufacturer: Pharmacy Value Alliance, LLC
Category: otc | Type: HUMAN OTC DRUG LABEL
Date: 20250103

ACTIVE INGREDIENTS: ISOPROPYL ALCOHOL 70 mL/100 mL
INACTIVE INGREDIENTS: WATER

68016-809 Pharmacy Value Alliance

Active ingredient

Isopropyl alcohol 70% v/v

Purpose

Antiseptic

Uses

- • first aid to decrease germs in minor cuts, scrapes and burns

Warnings

- For external use only.
- Flammable, keep away from fire or flame.

Do not use

- • with electrocautery procedures
- • longer than 1 week unless directed by a doctor

When using this product

- • do not get into eyes
- • do not apply over large areas of the body
- • in case of deep or puncture wounds, animal bites or serious burns, consult a doctor

Stop use and ask a doctor if

- • irritation and redness develop
- • condition gets worse or persists for more than 72 hours

Keep out of reach of children.

If accidentally swallowed, get medical help or contact a Poison Control Center right away.

Directions

- • apply to skin as needed
- • discard after single use

Other information

- • protect from freezing and avoid excessive heat
- • not made with natural rubber latex

Inactive ingredients

water

Manufacturing Information

Distributed by:

Pharmacy Value Alliance, LLC

407 East Lancaster Avenue, Wayne, PA 19087 USA

Packaged in China with components from Taiwan

REF: CDC090734
V1 RC20SXM